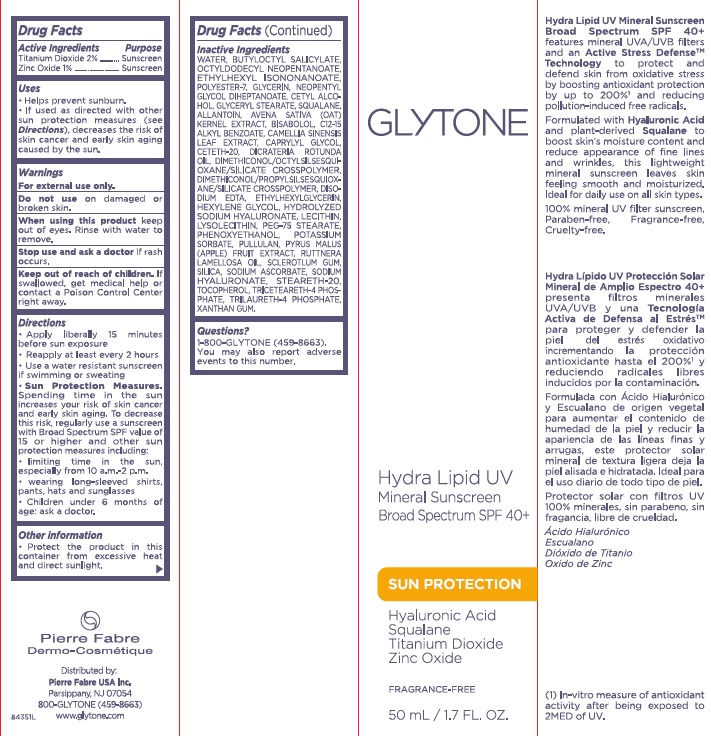 DRUG LABEL: Glytone Hydra Lipid UV Mineral Sunscreen
NDC: 64760-720 | Form: LOTION
Manufacturer: Pierre Fabre USA Inc.
Category: otc | Type: HUMAN OTC DRUG LABEL
Date: 20240429

ACTIVE INGREDIENTS: TITANIUM DIOXIDE 2 mg/50 mL; ZINC OXIDE 1 mg/50 mL
INACTIVE INGREDIENTS: OCTYLDODECYL NEOPENTANOATE; BUTYLOCTYL SALICYLATE; PHENOXYETHANOL; PEG-75 STEARATE; .BETA.-BISABOLOL; APPLE FRUIT OIL; HYDROGENATED SOYBEAN LECITHIN; CAMELLIA SINENSIS FLOWER; OAT KERNEL OIL; SODIUM ASCORBATE; POTASSIUM SORBATE; ALPHA-TOCOPHEROL, L-; WATER; ETHYLHEXYL ISONONANOATE; GLYCERIN; CETYL ALCOHOL; NEOPENTYL GLYCOL DIHEPTANOATE; DICRATERIA ROTUNDA OIL; SODIUM ACETYLATED HYALURONATE; DIMETHICONOL/PROPYLSILSESQUIOXANE/SILICATE CROSSPOLYMER (450000000 MW); DITETRACYCLINE TETRASODIUM EDETATE; TRILAURETH-4 PHOSPHATE; POLYESTER-7; C12-15 ALKYL ETHYLHEXANOATE; LOCUST BEAN GUM; GLYCERYL STEARATE SE; SQUALANE; ETHYLHEXYLGLYCERIN; HEXYLENE GLYCOL; HYDRATED SILICA; RUTTNERA LAMELLOSA OIL

Glytone Hydra Lipid UV Mineral Sunscreen SPF 40 PLUS

Purpose

Sunscreen

Active ingredients

Titanium Dioxide 2%

Zinc Oxide 1%

Uses

- Helps prevent sunburn.
- If used as directed with other sun protection measures (see Directions), decreases the risk of skin cancer and early skin aging caused by the sun.

Warnings

For external use only

Directions

- Apply liberally 15 minutes before sun exposure
- Reapply at least every 2 hours
- Use a water resistant sunscreen if swimming or sweating.

Sun Protection Measures. Spending time in the sun increases your risk of skin cancer and early skin aging. To decrease this risk, regularly use a sunscreen with a broad spectrum SPF of 15 or higher and other sun protection measures including:

- limit time in the sun, especially from 10 a.m. - 2 p.m.
- wear long-sleeve shirts, pants, hats, and sunglasses
- Children under 6 months: Ask a doctor

Other information

- Protect this product from excessive heat and direct sun.

Inactive ingredients

Water, Butyloctyl Salicylate, Octyldodecyl Neopentanoate, Ethylhexyl Isononanoate, Polyester-7, Glycerin, Neopentyl Glycol, Diheptanoate, Cetyl Alcohol, Glyceryl Stearate, Squalane, Phenoxyethanol, PEG-75 Stearate, Bisabolol, Hydrolyzed Sodium Hyaluronate, Pyrus Malus (Apple) Fruit Extract, C12-15 Alkyl Benzoate, Lysolecithin, Sclerotlum Gum, Dimethiconol/Octylsilsesquioxane/Silicate Crosspolymer, Allantoin, Ceteth-20, Steareth-20, Caprylyl Glycol, Triceteareth-4 Phosphate. Pullulan. Xanthan Gum, Sodium Hyaluronate, Dimethiconol/Propylsilsesquioxane/Silicate Crosspolymer
Disodium EDTA, Ethylhexylglycerin, Hexylene Glycol, Dicrateria Rotunda Oil, Ruttnera Lamellosa Oil, Lecithin, Silica, Camellia Sinensis Leaf Extract, Avena Sativa (Oat) Kernel Extract, Sodium Ascorbate, Potassium Sorbate, Tocopherol.

Questions or comments?

visit www.glytone.com or call toll-free 800-GLYTONE (459-8663)

Indications

Apply generously 15 minutes before sun exposure

etc

Keep out of reach of children.

If swallowed, call a Poison Control Center right away.

Do not use

On broken skin

Principal Display Panel - 50 mL Carton

GLYTONE

Hyda Lipid UV

Mineral Sunscreen

Broad spectrum SPF 40+

Sun Protection

Hyaluronic Acid

Squalane

Titanium Dioxide

Zinc Oxide

FRAGRANCE-FREE

50 mL / 1.7 FL. OZ.